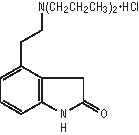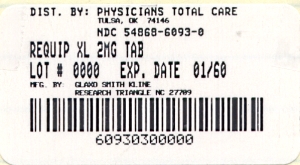 DRUG LABEL: REQUIP
NDC: 54868-6093 | Form: TABLET, FILM COATED, EXTENDED RELEASE
Manufacturer: Physicians Total Care, Inc.
Category: prescription | Type: HUMAN PRESCRIPTION DRUG LABEL
Date: 20111227

ACTIVE INGREDIENTS: ROPINIROLE HYDROCHLORIDE 2 mg/1 1
INACTIVE INGREDIENTS: CARBOXYMETHYLCELLULOSE SODIUM; SILICON DIOXIDE; GLYCERYL BEHENATE; HYDROGENATED CASTOR OIL; HYPROMELLOSES; LACTOSE MONOHYDRATE; MAGNESIUM STEARATE; MALTODEXTRIN; MANNITOL; POVIDONE

HIGHLIGHTS OF PRESCRIBING INFORMATION

These highlights do not include all the information needed to use REQUIP XL safely and effectively. See full prescribing information for REQUIP XL.
REQUIP XL (ropinirole extended-release tablets)
Initial U.S. Approval: 1997

1 INDICATIONS AND USAGE

REQUIP XL is an orally administered, non-ergoline dopamine agonist indicated for the treatment of signs and symptoms of idiopathic Parkinson’s disease. (1.1)

2 DOSAGE AND ADMINISTRATION

- REQUIP XL Tablets are taken once daily, with or without food. Tablets must be swallowed whole and must not be chewed, crushed, or divided. (2.1)
- The starting dose is 2 mg taken once daily for 1 to 2 weeks, followed by increases of 2 mg/day at 1 week or longer intervals as appropriate, depending on therapeutic response and tolerability, up to a maximally recommended dose of 24 mg/day. Patients should be assessed for therapeutic response and tolerability at a minimal interval of 1 week or longer after each dose increment. Caution should be exercised during dose titration because too rapid a rate of titration can lead to dose selection that does not provide additional benefit, but that increases the risk of adverse reactions. (2.2, 14.2)
- Patients may be switched directly from immediate-release ropinirole to REQUIP XL. The initial switching dose of REQUIP XL should most closely match the total daily dose of immediate-release ropinirole, see Table 1. (2.3)
- If REQUIP XL must be discontinued, it should be tapered gradually over a 7-day period. (2.2)

3 DOSAGE FORMS AND STRENGTHS

Tablets: 2 mg, 4 mg, 6 mg, 8 mg, and 12 mg (3)

4 CONTRAINDICATIONS

None

5 WARNINGS AND PRECAUTIONS

- Falling asleep during activities of daily living may occur, including the operation of motor vehicles, which sometimes resulted in accidents. Sudden onset of sleep may occur without apparent warning or daytime drowsiness. Sedating medications (such as alcohol or CNS depressants), the presence of sleeping disorders, or other medications that increase plasma levels of ropinirole, may increase the risk of somnolence or falling asleep while engaged in activities of daily living. Before initiating treatment, patients should be advised of the potential of sudden onset of sleep or to develop drowsiness and asked about risk factors they may have. If a patient develops sudden onset of sleep during activities that require active participation (e.g., conversations, eating, etc.) and/or cannot avoid high-risk activities in the future, REQUIP XL should ordinarily be discontinued. (5.1)
- Syncope, sometimes associated with bradycardia, may occur. (5.2)
- Symptomatic hypotension (including postural/orthostatic hypotension) may occur, especially during dose escalation. (5.3)
- Elevation of blood pressure and changes in heart rate may occur. (5.4)
- Hallucination may occur. (5.5)
- Dyskinesia may be caused or exacerbated. Decreasing the L-dopa dose may lessen or eliminate this side effect. (5.6)

6 ADVERSE REACTIONS

- Most common adverse reactions (incidence ≥5% and greater than placebo) in advanced Parkinson’s disease with concomitant L-dopa were dyskinesia, nausea, dizziness, hallucination, somnolence, abdominal pain/discomfort, and orthostatic hypotension. (6.1)
- Most common adverse reactions (incidence ≥5%) in early Parkinson’s disease without L-dopa were nausea, somnolence, abdominal pain/discomfort, dizziness, headache, and constipation. (6.1)
  To report SUSPECTED ADVERSE REACTIONS, contact GlaxoSmithKline at 1-888-825-5249 or FDA at 1-800-FDA-1088 or www.fda.gov/medwatch.

7 DRUG INTERACTIONS

- CYP1A2 is the major enzyme responsible for the metabolism of ropinirole. Thus inhibitors (e.g., ciprofloxacin, fluvoxamine) or inducers (e.g., omeprazole or smoking) of CYP1A2 may alter the clearance of ropinirole. Adjustment of dosage of REQUIP XL may be required. (7.1)
- Higher doses of estrogens, usually associated with hormone replacement therapy (HRT), reduced oral clearance of ropinirole. Starting or stopping HRT treatment may require adjustment of dosage of REQUIP XL. (7.3)
- Dopamine antagonists, such as neuroleptics (e.g., phenothiazines, butyrophenones, thioxanthenes) or metoclopramide, may diminish effectiveness of ropinirole. (7.4)

8 USE IN SPECIFIC POPULATIONS

Pregnancy: REQUIP XL should be used during pregnancy only if the potential benefit outweighs the potential risk to the fetus. (8.1)

Revised: April 2009

RXL:4PI

FULL PRESCRIBING INFORMATION

1 INDICATIONS AND USAGE

1.1 Parkinson’s Disease

REQUIP XL (ropinirole extended-release tablets) is indicated for the treatment of the signs and symptoms of idiopathic Parkinson’s disease.

2 DOSAGE AND ADMINISTRATION

2.1 General Dosing Considerations

- REQUIP XL Extended-Release Tablets are taken once daily, with or without food. Taking REQUIP XL with food may reduce the occurrence of nausea; this has not been established in controlled clinical trials [see Clinical Pharmacology (12.3)].
- Tablets must be swallowed whole and must not be chewed, crushed, or divided.
- If a significant interruption in therapy with REQUIP XL has occurred, retitration of therapy may be warranted.

2.2 Dosing for Parkinson’s Disease

The starting dose is 2 mg taken once daily for 1 to 2 weeks, followed by increases of 2 mg/day at 1-week or longer intervals as appropriate, depending on therapeutic response and tolerability, up to a maximally recommended dose of 24 mg/day.

In clinical trials, dosage was initiated at 2 mg/day and gradually titrated based on individual therapeutic response and tolerability. Doses greater than 24 mg/day have not been studied in clinical trials. Patients should be assessed for therapeutic response and tolerability at a minimal interval of 1 week or longer after each dose increment. Caution should be exercised during dose titration because too rapid a rate of titration may lead to dose selection that may not provide additional benefit, but that may increase the risk of adverse reactions [see Clinical Studies (14.2)]. Due to the flexible dosing design used in clinical studies, specific dose response information could not be determined.

When REQUIP XL is administered as adjunct therapy to L-dopa, the concurrent dose of L-dopa may be decreased gradually as tolerated. In the placebo-controlled advanced Parkinson’s disease study, the L-dopa dose was reduced once patients reached a dose of REQUIP XL of 8 mg/day. Overall, L-dopa dose reduction was sustained in 93% of patients treated with REQUIP XL and in 72% of patients on placebo. On average the L-dopa dose was reduced by 34% in patients treated with REQUIP XL [see Clinical Studies (14)].

REQUIP XL should be discontinued gradually over a 7-day period.

2.3 Switching From Immediate-Release Ropinirole Tablets to REQUIP XL

Patients may be switched directly from immediate-release ropinirole to REQUIP XL Tablets. The initial dose of REQUIP XL should most closely match the total daily dose of the immediate-release formulation of REQUIP, as shown in Table 1.

Table 1. Conversion from Immediate-Release REQUIP to REQUIP XL
Immediate-Release Ropinirole Tablets; Total Daily Dose (mg) | REQUIP XL Tablets; Total Daily Dose (mg)
0.75 to 2.25 | 2
3 to 4.5 | 4
6 | 6
7.5 to 9 | 8
12 | 12
15 to 18 | 16
21 | 20
24 | 24

Following conversion to REQUIP XL, the dose may be adjusted depending on therapeutic response and tolerability[see Dosage and Administration (2.2)].

3 DOSAGE FORMS AND STRENGTHS

- 2 mg, pink, biconvex, capsule-shaped, film-coated, tablets debossed with “GS” and “3V2”
- 4 mg, light brown, biconvex, capsule-shaped, film-coated, tablets debossed with “GS” and “WXG”
- 6 mg, white, biconvex, capsule-shaped, film-coated, tablets debossed with “GS” and “11F”
- 8 mg, red, biconvex, capsule-shaped, film-coated, tablets debossed with “GS” and “5CC”
- 12 mg, green, biconvex, capsule-shaped, film-coated, tablets debossed with “GS” and “YX7”

4 CONTRAINDICATIONS

None.

5 WARNINGS AND PRECAUTIONS

5.1 Falling Asleep During Activities of Daily Living

Patients treated with ropinirole have reported falling asleep while engaged in activities of daily living, including the operation of motor vehicles, which sometimes resulted in accidents. Although many of these patients reported somnolence while on ropinirole, some perceived that they had no warning signs such as excessive drowsiness, and believed that they were alert immediately prior to the event. Some of these events have been reported more than 1 year after initiation of treatment.

Among the 613 patients who received REQUIP XL in clinical trials, there were 5 cases of sudden onset of sleep and 2 cases of motor vehicle accident in which it is not known if falling asleep was a contributing factor.

During the 6-month trial in advanced Parkinson’s disease, somnolence was reported in 7% (14 of 202) of patients receiving REQUIP XL compared with 4% (7 of 191) of patients receiving placebo. During the 36-week trial in early Parkinson’s disease, somnolence was reported in 11% (16 of 140) of patients receiving REQUIP XL compared with 15% (22 of 149) of patients receiving the immediate-release formulation of REQUIP [see Adverse Reactions (6)]. However, because dose-response was not systematically studied with REQUIP XL, the occurrence of somnolence at the highest recommended doses may be higher than these reported frequencies [see Adverse Reactions (6)].

Many clinical experts believe that falling asleep while engaged in activities of daily living always occurs in a setting of preexisting somnolence, although patients may not give such a history. For this reason, prescribers should continually reassess patients for drowsiness or sleepiness, especially since some of the events occur well after the start of treatment. Prescribers should also be aware that patients may not acknowledge drowsiness or sleepiness until directly questioned about drowsiness or sleepiness during specific activities.

Before initiating treatment with REQUIP XL, patients should be advised of the potential to develop drowsiness and specifically asked about factors that may increase the risk with REQUIP XL such as concomitant sedating medications, the presence of sleep disorders, and concomitant medications that increase ropinirole plasma levels (e.g., ciprofloxacin) [see Drug Interactions (7.1)]. If a patient develops significant daytime sleepiness or episodes of falling asleep during activities that require active participation (e.g., driving a motor vehicle, conversations, eating, etc.), REQUIP XL should ordinarily be discontinued [see Dosage and Administration for guidance in discontinuing REQUIP XL (2.2)]. If a decision is made to continue REQUIP XL, patients should be advised to not drive and to avoid other potentially dangerous activities. There is insufficient information to establish that dose reduction will eliminate episodes of falling asleep while engaged in activities of daily living.

5.2 Syncope

Syncope, sometimes associated with bradycardia, was observed during treatment with ropinirole in Parkinson’s disease patients.

In a placebo-controlled study involving patients with advanced Parkinson’s disease, syncope occurred in 2 of the 202 patients (1%) who received REQUIP XL, and in none of the 191 patients who received placebo.

Because the study of REQUIP XL excluded patients with significant cardiovascular disease, it is not known to what extent the estimated incidence figure applies to patients with Parkinson’s disease in clinical practice. Therefore, patients with significant cardiovascular disease should be treated with caution.

5.3 Hypotension

Dopamine agonists, in clinical studies and clinical experience, appear to impair the systemic regulation of blood pressure, with resulting postural hypotension, especially during dose escalation. In addition, patients with Parkinson’s disease appear to have an impaired capacity to respond to a postural challenge. For these reasons, patients being treated with dopaminergic agonists ordinarily (1) require careful monitoring for signs and symptoms of postural hypotension, especially during dose escalation, and (2) should be informed of this risk [see Patient Counseling Information (17.2)].

In a placebo-controlled trial involving patients with advanced Parkinson’s disease, hypotension was reported as an adverse event in 5 of 202 patients (2%) receiving REQUIP XL and in none of the 191 patients receiving placebo. Orthostatic hypotension was reported as an adverse event in 5% of patients receiving REQUIP XL, and in 1% of placebo recipients.

An analysis of the randomized, double-blinded, placebo-controlled study in advanced Parkinson’s disease was conducted using a variety of adverse event terms possibly suggestive of hypotension, including hypotension, orthostatic hypotension, dizziness, vertigo, and blood pressure decreased. This analysis showed a higher incidence of these events with REQUIP XL (7%, 15 of 202) vs. placebo (3%, 6 of 191). This increased incidence was observed in a setting in which patients were very carefully titrated, and patients with clinically relevant cardiovascular disease or symptomatic orthostatic hypotension at baseline had been excluded from this study.

Orthostatic vital signs (semi-supine to standing) were monitored throughout the study in the advanced Parkinson’s disease study and changes related to REQUIP XL (compared with placebo) from baseline were assessed.

The frequency of any orthostatic hypotension at any time during the study was 38% for REQUIP XL vs. 31% for placebo for mild to moderate systolic blood pressure decrements (≥20 mm Hg), 63% for REQUIP XL vs. 58% for placebo for mild to moderate diastolic blood pressure decrements (≥10 mm Hg), 10% for REQUIP XL vs. 7% for placebo for severe diastolic blood pressure decrements (≥20 mm Hg), and 23% for REQUIP XL vs. 19% for placebo for mild to moderate combined systolic and diastolic blood pressure decrements.

Significant decrements in blood pressure unrelated to standing were also reported in some patients taking REQUIP XL. In the semi-supine position, the frequency was 10% for REQUIP XL vs. 8% for placebo for severe systolic blood pressure decrease (≥40 mm Hg), and was 25% for REQUIP XL vs. 21% for placebo for severe diastolic blood pressure decrease (≥20 mm Hg).

The increased incidence for hypotension and/or orthostatic hypotension was observed in both the titration and maintenance phases and in some cases persisted into the maintenance period after developing in the titration phase.

5.4 Elevation of Blood Pressure and Changes in Heart Rate

In the placebo-controlled study in advanced Parkinson’s disease, there were no clear effects of REQUIP XL on average changes in blood pressure or heart rate compared with placebo. However, there was an increased incidence of patients treated with REQUIP XL who met various outlier criteria, as described below.

In the semi-supine position, the frequency was 8% for REQUIP XL vs. 5% for placebo for severe systolic blood pressure increase (≥40 mm Hg). In the standing position, the frequency was 9% for REQUIP XL vs. 6% for placebo for severe systolic blood pressure increase (≥40 mm Hg).

In the semi-supine position, the frequency was 23% for REQUIP XL vs. 18% for placebo for moderate pulse increase (≥15 beats/minute), and 19% for REQUIP XL vs. 17% for placebo for moderate pulse decrease (≥15 beats/minute). In the standing position, the frequency was 2% for REQUIP XL vs. <1% for placebo for severe pulse increase (≥30 beats/minute), and 24% for REQUIP XL vs. 19% for placebo for moderate pulse decrease (≥15 beats/minute).

The increased incidence for various elevations of systolic and/or diastolic blood pressure and/or changes in pulse was observed in both the titration and maintenance phases as well as persisting into the maintenance period after developing in the titration phase.

Elevation of blood pressure and/or changes in heart rate in patients taking REQUIP XL should be considered when treating patients with cardiovascular disease.

5.5 Hallucination

In the double-blind, placebo-controlled, advanced Parkinson’s disease trial 8% (17 of 202) of patients receiving REQUIP XL reported hallucination compared with 2% (4 of 191) patients receiving placebo. Hallucination led to discontinuation of treatment in 2% (4 of 202) of patients on REQUIP XL and 1% (2 of 191) of patients on placebo.

The incidence of hallucination is increased in patients over age 65. Coadministration of entacapone and L-dopa with ropinirole may also increase the risk of hallucination. In a placebo-controlled clinical trial, hallucination occurred in 0 of 43 patients taking entacapone plus L-dopa, in 9 of 155 patients taking REQUIP XL plus L-dopa (6%), and in 7 of 47 patients taking entacapone with REQUIP XL plus L-dopa (15%).

5.6 Dyskinesia

REQUIP XL may potentiate the dopaminergic side effects of L-dopa and may cause and/or exacerbate preexisting dyskinesia in patients treated with L-dopa for Parkinson’s disease. Decreasing the dose of a dopaminergic drug may ameliorate this side effect.

5.7 Major Psychotic Disorders

Patients with a major psychotic disorder should ordinarily not be treated with REQUIP XL because of the risk of exacerbating the psychosis. In addition, many treatments for psychosis may decrease the effectiveness of REQUIP XL [see Drug Interactions (7.4)].

5.8 Events Reported With Dopaminergic Therapy

Withdrawal-Emergent Hyperpyrexia and Confusion: Although not reported during the clinical development of ropinirole, a symptom complex resembling the neuroleptic malignant syndrome (characterized by elevated temperature, muscular rigidity, altered consciousness, and autonomic instability), with no other obvious etiology, has been reported in association with rapid dose reduction, withdrawal of, or changes in dopaminergic therapy. Therefore, it is recommended that the dose be tapered at the end of treatment with REQUIP XL as a prophylactic measure [see Dosage and Administration (2.2)].

Fibrotic Complications: Cases of retroperitoneal fibrosis, pulmonary infiltrates, pleural effusion, pleural thickening, pericarditis, and cardiac valvulopathy have been reported in some patients treated with ergot-derived dopaminergic agents. While these complications may resolve when the drug is discontinued, complete resolution does not always occur.

Although these adverse reactions are believed to be related to the ergoline structure of these compounds, whether other, nonergot-derived dopamine agonists, such as REQUIP or REQUIP XL, can cause them is unknown.

A small number of reports have been received of possible fibrotic complications, including pleural effusion, pleural fibrosis, interstitial lung disease, and cardiac valvulopathy, in the development program and postmarketing experience for ropinirole. In the clinical development program (N = 613), 2 patients treated with REQUIP XL had pleural effusion. While the evidence is not sufficient to establish a causal relationship between ropinirole and these fibrotic complications, a contribution of ropinirole cannot be completely ruled out in rare cases.

Melanoma: Some epidemiologic studies have shown that patients with Parkinson’s disease have a higher risk (perhaps 2- to 4-fold higher) of developing melanoma than the general population. Whether the observed increased risk was due to Parkinson’s disease or other factors, such as drugs used to treat Parkinson’s disease, was unclear. Ropinirole is one of the dopamine agonists used to treat Parkinson’s disease. Although ropinirole has not been associated with an increased risk of melanoma specifically, its potential role as a risk factor has not been systematically studied. In the clinical development program (N = 613), one patient treated with REQUIP XL and also levodopa/carbidopa developed melanoma. Patients using REQUIP XL should be made aware of these results and undergo periodic dermatologic screening.

5.9 Retinal Pathology

Human: Because of observations made in albino rats (see below), ocular electroretinogram (ERG) assessments were conducted during a 2-year, double-blind, multicenter, flexible-dose, l-dopa controlled clinical study of immediate-release ropinirole in patients with Parkinson’s disease. A total of 156 patients (78 on immediate-release ropinirole, mean dose 11.9 mg/day and 78 on l-dopa, mean dose 555.2 mg/day) were evaluated for evidence of retinal dysfunction through electroretinograms. There was no clinically meaningful difference between the treatment groups in retinal function over the duration of the study.

Albino Rats: Retinal degeneration was observed in albino rats in the 2-year carcinogenicity study at all doses tested (equivalent to 0.6 to 20 times the maximum recommended human dose (MRHD) of 24 mg/day on a mg/m^2 basis), but was statistically significant at the highest dose (50 mg/kg/day). Retinal degeneration was not observed in pigmented rats after 3 months in a 2-year carcinogenicity study in albino mice, or in 1-year studies in monkeys or albino rats. The potential significance of this effect for humans has not been established, but cannot be disregarded because disruption of a mechanism that is universally present in vertebrates (e.g., disk shedding) may be involved.

5.10 Binding to Melanin

Ropinirole binds to melanin-containing tissues (i.e., eyes, skin) in pigmented rats. After a single dose, long-term retention of drug was demonstrated, with a half-life in the eye of 20 days.

6 ADVERSE REACTIONS

The following adverse reactions are described in more detail in the Warnings and Precautions section of the label:

- Falling asleep during activities of daily living (5.1)
- Syncope (5.2)
- Symptomatic hypotension, hypotension, postural/orthostatic hypotension (5.3)
- Elevation of blood pressure and changes in heart rate (5.4)
- Hallucination (5.5)
- Dyskinesia (5.6)
- Major psychotic disorders (5.7)
- Events with dopaminergic therapy (5.8)
- Retinal pathology (5.9)

6.1 Clinical Trial Experience

Because clinical trials are conducted under widely varying conditions, adverse reaction rates observed in the clinical trials of a drug cannot be directly compared with rates in the clinical trials of another drug (or of another development program of a different formulation of the same drug) and may not reflect the rates observed in practice.

During the premarketing development of REQUIP XL, patients with advanced Parkinson’s disease received REQUIP XL or placebo as adjunctive therapy in 1 clinical trial. In a second trial, patients with early Parkinson’s disease were treated with REQUIP XL or the immediate-release formulation of REQUIP without L-dopa.

Advanced Parkinson’s Disease (With L-dopa): The most commonly observed adverse reactions (≥5% and numerically greater than placebo) in the 24-week, double-blind, placebo-controlled trial for the treatment of advanced Parkinson’s disease during treatment with REQUIP XL were, in order of decreasing incidence: dyskinesia, nausea, dizziness, hallucination, somnolence, abdominal pain/discomfort, and orthostatic hypotension.

Approximately 6% of 202 patients treated with REQUIP XL discontinued treatment due to adverse event(s) compared with 5% of 191 patients who received placebo. The adverse event most commonly causing discontinuation of treatment with REQUIP XL was hallucination (2%).

Table 2 lists adverse reactions that occurred with a frequency of at least 2% (and were numerically greater than placebo) in patients with advanced Parkinson’s disease treated with REQUIP XL who participated in the 26-week, double-blind, placebo-controlled study. In this study, either REQUIP XL or placebo was used as an adjunct to L -dopa. Adverse reactions were generally mild or moderate in intensity.

Table 2. Treatment-Emergent Adverse Reaction Incidence in a Double-Blind, Placebo-Controlled Trial in Advanced Stage Parkinson’s Disease (With L-dopa) (Events ≥2% of Patients Treated with REQUIP XL and >% with Placebo)
Body System/Adverse Reaction | REQUIP XL; (n = 202); % | Placebo; (n = 191); %
Ear and labyrinth disorders
Vertigo | 4 | 2
Gastrointestinal disorders
Nausea | 11 | 4
Constipation | 4 | 2
Abdominal pain/discomfort | 6 | 3
Diarrhea | 3 | 2
Dry mouth | 2 | <1
General disorders
Edema peripheral | 4 | 1
Injury, poisoning, and procedural complications
Fall* | 2 | 1
Musculoskeletal and connective tissue disorders
Back pain | 3 | 2
Nervous system disorders
Dyskinesia* | 13 | 3
Dizziness | 8 | 3
Somnolence | 7 | 4
Psychiatric disorders
Hallucination | 8 | 2
Anxiety | 2 | 1
Vascular disorders
Orthostatic hypotension | 5 | 1
Hypotension | 2 | 0
Hypertension* | 3 | 2

*Dose-related.

Although this study was not designed for optimally characterizing dose-related adverse reactions, there was a suggestion (based upon comparison of incidence of adverse reactions across dose ranges for REQUIP XL and placebo) that the incidence for dyskinesia, hypertension, and fall was dose-related to REQUIP XL.

The incidence for many adverse reactions with REQUIP XL treatment was increased relative to placebo (i.e., REQUIP XL % - Placebo % = treatment difference ≥2%) in either the titration or maintenance phases of the study. During the titration phase, an increased incidence (shown in descending order of % treatment difference) was observed for dyskinesia, nausea, abdominal pain/discomfort, orthostatic hypotension, dizziness, vertigo, hypertension, peripheral edema, and dry mouth. During the maintenance phase, an increased incidence was observed for dyskinesia, nausea, dizziness, hallucination, somnolence, fall, hypertension, abnormal dreams, constipation, chest pain, bronchitis, and nasopharyngitis. Some adverse reactions developing in the titration phase persisted (≥7 days) into the maintenance phase. These “persistent” adverse reactions included dyskinesia, hallucination, orthostatic hypotension, and dry mouth.

The incidence of adverse reactions was not clearly different between women and men.

Early Parkinson’s Disease (Without L-dopa): The most commonly observed adverse reactions (≥5%) in the 36-week early Parkinson’s disease trial during treatment with REQUIP XL were, in order of decreasing incidence: nausea (19%), somnolence (11%), abdominal pain/discomfort (7%), dizziness (6%), headache (6%), and constipation (5%). The type of adverse reactions and the frequency (i.e. incidence) with which they occurred were generally similar over the whole treatment period in this study of early Parkinson’s disease patients who were initially treated with REQUIP XL or the immediate-release formulation of REQUIP and subsequently crossed over to treatment with the other formulation.

During the titration phase, an increased incidence with REQUIP XL compared with the immediate-release formulation of REQUIP (i.e., REQUIP XL % - REQUIP IR % = treatment difference ≥2%), shown in descending order of % treatment difference, was observed for: constipation, hallucination, vertigo, abdominal pain/discomfort, nausea, vomiting, fall, headache, diarrhea, pyrexia, and flatulence. During the maintenance phase, an increased incidence was observed for fall, myalgia, and sleep disorder. Several adverse reactions developing in the titration phase persisted (≥7 days) into the maintenance phase. These “persistent” adverse reactions included: constipation, hallucination, muscle spasms, flatulence, insomnia, sleep disorder, abdominal pain/discomfort, cough, and nasopharyngitis.

6.2 Adverse Reactions Observed During the Clinical Development of the Immediate-Release Formulation of REQUIP for Parkinson’s Disease (Advanced and Early)

Because clinical trials are conducted under widely varying conditions, adverse reaction rates observed in the clinical trials of a drug cannot be directly compared to rates in the clinical trials of another drug (or of another development program of a different formulation of the same drug) and may not reflect the rates observed in practice.

In patients with advanced Parkinson’s disease who were treated with the immediate-release formulation of REQUIP, the most common adverse reactions (≥5% treatment difference from placebo; presented in order of decreasing treatment difference frequency) were dyskinesia (21%), somnolence (12%), nausea (12%), dizziness (10%), confusion (7%), hallucinations (6%), headache (5%), and increased sweating (5%). In patients with early Parkinson’s disease who were treated with the immediate-release formulation of REQUIP, the most common adverse reactions (≥5% treatment difference from placebo; presented in order of decreasing treatment difference frequency) were nausea (38%), somnolence (34%), dizziness (18%), syncope (11%), viral infection (8%), fatigue (7%), leg edema (6%), asthenia (5%), and dyspepsia (5%).

7 DRUG INTERACTIONS

7.1 P450 Interaction

In vitro metabolism studies showed that CYP1A2 is the major enzyme responsible for the metabolism of ropinirole. There is thus the potential for inducers or inhibitors of this enzyme to alter the clearance of ropinirole. Therefore, if therapy with a drug known to be a potent inducer or inhibitor of CYP1A2 is stopped or started during treatment with ropinirole, adjustment of the dose of ropinirole may be required.

Coadministration of ciprofloxacin, an inhibitor of CYP1A2, with immediate-release ropinirole increased the AUC of ropinirole by 84% on average and Cmax by 60% [see Clinical Pharmacology (12.3)].

Cigarette smoking is expected to increase the clearance of ropinirole since CYP1A2 is known to be induced by smoking. In one study in patients with Restless Legs Syndrome, cigarette smokers had an approximate 30% lower Cmax and a 38% lower AUC than did nonsmokers, when those parameters were normalized for dose.

There is no evidence of interaction between ropinirole and other CYP1A2 substrates (e.g., theophylline).

Ropinirole and its circulating metabolites do not inhibit or induce P450 enzymes therefore ropinirole is unlikely to affect the pharmacokinetics of other drugs by a P450 mechanism [see Clinical Pharmacology (12.3)].

7.2 L-dopa

Coadministration of carbidopa + L-dopa (SINEMET®*) with immediate-release ropinirole had no effect on the steady-state pharmacokinetics of ropinirole. Oral administration of immediate-release ropinirole increased mean steady-state Cmax of L-dopa by 20%, but its AUC was unaffected [see Clinical Pharmacology (12.3)].

7.3 Estrogens

Population pharmacokinetic analysis revealed that higher doses of estrogens (usually associated with hormone replacement therapy [HRT]) reduced the oral clearance of ropinirole by approximately 35%. Dosage adjustment is not needed for initiating REQUIP XL in patients on estrogen therapy because patients are individually titrated with REQUIP XL to tolerance or adequate effect. If estrogen therapy is stopped or started during treatment with REQUIP XL, then adjustment of the dose of REQUIP XL may be required.

7.4 Dopamine Antagonists

Since ropinirole is a dopamine agonist, it is possible that dopamine antagonists such as neuroleptics (e.g., phenothiazines, butyrophenones, thioxanthenes) or metoclopramide may diminish the effectiveness of REQUIP XL. Patients with a history or presence of major psychotic disorders should be treated with dopamine agonists only if the potential benefits outweigh the risks.

8 USE IN SPECIFIC POPULATIONS

8.1 Pregnancy

Pregnancy Category C. There are no adequate and well-controlled studies using ropinirole in pregnant women. REQUIP XL should be used during pregnancy only if the potential benefit outweighs the potential risk to the fetus.

In animal reproduction studies, ropinirole has been shown to have adverse effects on embryo-fetal development, including teratogenic effects. Treatment of pregnant rats with ropinirole during organogenesis resulted in decreased fetal body weight, increased fetal death, and digital malformations at 24, 36, and 60 times the MRHD, respectively. The combined administration of ropinirole at 8 times the MRHD and a clinically relevant dose of L-dopa to pregnant rabbits during organogenesis produced a greater incidence and severity of fetal malformations (primarily digit defects) than were seen in the offspring of rabbits treated with L-dopa alone. In a perinatal-postnatal study in rats, impaired growth and development of nursing offspring and altered neurological development of female offspring were observed when dams were treated with 4 times the MRHD.

8.3 Nursing Mothers

Ropinirole inhibits prolactin secretion in humans and could potentially inhibit lactation.

Ropinirole has been detected in the milk of lactating rats. Although many drugs are excreted in human milk, transfer of ropinirole into human milk has not been demonstrated. Due to the potential for serious adverse reactions in nursing infants, a decision should be made whether to discontinue nursing or to discontinue the drug, taking into account the importance of ropinirole to the mother.

8.4 Pediatric Use

Safety and effectiveness in the pediatric population have not been established.

8.5 Geriatric Use

Dosage adjustment is not necessary in the elderly (above 65 years), as the dose of REQUIP XL is to be individually titrated to clinical response [see Clinical Pharmacology (12.3)]. Pharmacokinetic studies conducted in patients demonstrated that oral clearance of ropinirole is reduced by 15% in patients above 65 years of age compared to younger patients.

Of the total number of patients who participated in clinical trials of REQUIP XL for Parkinson’s disease, 387 patients were 65 and over and 107 patients were 75 and over. Among patients receiving REQUIP XL, hallucination was more common in elderly subjects (10%) compared with non-elderly subjects (2%). The incidence of overall adverse events increased with increasing age for both patients receiving REQUIP XL and placebo.

8.6 Renal Impairment

No dosage adjustment of ropinirole is needed in patients with moderate renal impairment (creatinine clearance of 30 to 50 mL/min). The use of ropinirole in patients with severe renal impairment has not been studied.

8.7 Hepatic Impairment

The pharmacokinetics of ropinirole have not been studied in patients with hepatic impairment. Since patients with hepatic impairment may have higher plasma levels and lower clearance, ropinirole should be titrated with caution in these patients.

9 DRUG ABUSE AND DEPENDENCE

9.1 Controlled Substance

Ropinirole is not a controlled substance.

9.3 Dependence

Animal studies and human clinical trials with ropinirole did not reveal any potential for drug-seeking behavior or physical dependence.

10 OVERDOSAGE

10.1 Human Overdose Experience

In the Parkinson’s disease program, there have been patients who accidentally or intentionally took more than their prescribed dose of ropinirole. The largest overdose reported with immediate-release ropinirole in clinical trials was 435 mg taken over a 7-day period (62.1 mg/day). Of patients who received a dose greater than 24 mg/day, reported symptoms included adverse events commonly reported during dopaminergic therapy (nausea, dizziness), as well as visual hallucination, hyperhidrosis, claustrophobia, chorea, palpitations, asthenia, and nightmares. Additional symptoms reported for doses of 24 mg or less or for overdoses of unknown amount included vomiting, increased coughing, fatigue, syncope, vasovagal syncope, dyskinesia, agitation, chest pain, orthostatic hypotension, somnolence, and confusional state.

10.2 Overdose Management

The symptoms of overdose with ropinirole are generally related to its dopaminergic activity; these symptoms may be alleviated by appropriate treatment with dopamine antagonists such as neuroleptics or metoclopramide. General supportive measures are recommended. Vital signs should be maintained, if necessary. Removal of any unabsorbed material (e.g., by gastric lavage) may be considered.

11 DESCRIPTION

REQUIP (ropinirole) is an orally administered non-ergoline dopamine agonist. It is supplied as the hydrochloride salt of ropinirole 4-[2-(dipropylamino)ethyl]-1,3-dihydro-2H-indol-2-one and has an empirical formula of C16H24N2O•HCl. The molecular weight is 296.84 (260.38 as the free base).

The structural formula is:

Ropinirole hydrochloride is a white to yellow solid with a melting range of 243° to 250°C and a solubility of 133 mg/mL in water.

REQUIP XL Extended-Release Tablets are formulated as a three-layered tablet with a central, active-containing, slow-release layer, and 2 placebo outer layers acting as barrier layers which control the surface area available for drug release. Each biconvex, capsule-shaped tablet contains 2.28 mg, 4.56 mg, 6.84 mg, 9.12 mg, or 13.68 mg ropinirole hydrochloride equivalent to ropinirole 2 mg, 4 mg, 6 mg, 8 mg, or 12 mg, respectively. Inactive ingredients consist of carboxymethylcellulose sodium, colloidal silicon dioxide, glyceryl behenate, hydrogenated castor oil, hypromellose, lactose monohydrate, magnesium stearate, maltodextrin, mannitol, povidone, and one or more of the following: FD&C Yellow No. 6 aluminum lake, FD&C Blue No. 2 aluminum lake, ferric oxides (black, red, yellow), polyethylene glycol 400, titanium dioxide.

12 CLINICAL PHARMACOLOGY

12.1 Mechanism of Action

Ropinirole is a non-ergoline dopamine agonist with high relative in vitro specificity and full intrinsic activity at the D2 and D3 dopamine receptor subtypes, binding with higher affinity to D3 than to D2 or D4 receptor subtypes.

Ropinirole has moderate in vitro affinity for opioid receptors. Ropinirole and its metabolites have negligible in vitro affinity for dopamine D1, 5-HT1, 5-HT2, benzodiazepine, GABA, muscarinic, alpha1-, alpha2-, and beta-adrenoreceptors.

The precise mechanism of action of ropinirole as a treatment for Parkinson’s disease is unknown, although it is believed to be due to stimulation of postsynaptic dopamine D2-type receptors within the caudate-putamen in the brain. This conclusion is supported by studies that show that ropinirole improves motor function in various animal models of Parkinson’s disease. In particular, ropinirole attenuates the motor deficits induced by lesioning the ascending nigrostriatal dopaminergic pathway with the neurotoxin 1-methyl-4-phenyl-1,2,3,6-tetrahydropyridine (MPTP) in primates. The relevance of D3 receptor binding in Parkinson’s disease is unknown.

12.2 Pharmacodynamics

Clinical experience with dopamine agonists, including ropinirole, suggests an association with impaired ability to regulate blood pressure with resulting postural hypotension, especially during dose escalation. In some subjects in clinical trials, blood pressure changes were associated with the emergence of orthostatic symptoms, bradycardia, and, in one case in a healthy volunteer, transient sinus arrest with syncope.

The mechanism of postural hypotension induced by ropinirole is presumed to be due to a D2-mediated blunting of the noradrenergic response to standing and subsequent decrease in peripheral vascular resistance. Nausea is a common concomitant symptom of orthostatic signs and symptoms.

At oral doses as low as 0.2 mg, ropinirole suppressed serum prolactin concentrations in healthy male volunteers.

Immediate-release ropinirole had no dose-related effect on ECG wave form and rhythm in young, healthy, male volunteers in the range of 0.01 to 2.5 mg. Immediate-release ropinirole had no dose- or exposure-related effect on mean QT intervals in healthy male and female volunteers titrated to doses up to 4 mg/day. The effect of ropinirole on QTc intervals at higher exposures achieved either due to drug interactions, hepatic impairment, or at higher doses has not been systematically evaluated.

12.3 Pharmacokinetics

Absorption: In clinical studies with immediate-release ropinirole, over 88% of a radiolabeled dose was recovered in urine, and the absolute bioavailability was 45% to 55%, indicating approximately 50% first-pass effect.

Ropinirole displayed linear kinetics up to doses of 24 mg/day (8 mg immediate-release, 3 times a day). Increase in systemic exposure of ropinirole following oral administration of 2 to 12 mg of REQUIP XL was approximately dose-proportional. For REQUIP XL, steady-state concentrations of ropinirole are expected to be achieved within 4 days of dosing.

Relative bioavailability of REQUIP XL Extended-Release Tablets compared with immediate-release tablets was approximately 100%. In a repeat-dose study in patients with Parkinson’s disease using REQUIP XL 8 mg, the dose-normalized AUC(0-24) and Cmin for REQUIP XL and immediate-release ropinirole were similar. Dose-normalized Cmax was, on average, 12% lower for REQUIP XL than for the immediate-release formulation and the median time-to-peak concentration was 6 to 10 hours. In a single-dose study, administration of REQUIP XL to healthy volunteers with food (i.e., high-fat meal) increased AUC by approximately 30% and Cmax by approximately 44%, compared with dosing under fasted conditions. In a repeat-dose study in patients with Parkinson’s disease, food (i.e., high-fat meal) increased AUC by approximately 20% and Cmax by approximately 44%; Tmax was prolonged by 3 hours (median prolongation) compared with dosing under fasted conditions [see Dosage and Administration (2.1)].

Distribution: Ropinirole is widely distributed throughout the body, with an apparent volume of distribution of 7.5 L/kg (cv = 32%). It is up to 40% bound to plasma proteins and has a blood-to-plasma ratio of 1:1.

Metabolism: Ropinirole is extensively metabolized by the liver. The major metabolic pathways are N-despropylation and hydroxylation to form the inactive N-despropyl metabolite and hydroxy metabolites. The N-despropyl metabolite is converted to carbamyl glucuronide, carboxylic acid, and N-despropyl hydroxy metabolites. The hydroxy metabolite of ropinirole is rapidly glucuronidated.

In vitro studies indicate that the major cytochrome P450 isozyme involved in the metabolism of ropinirole is CYP1A2, an enzyme known to be induced by smoking and omeprazole, and inhibited by, for example, fluvoxamine, mexiletine, and the older fluoroquinolones such as ciprofloxacin and norfloxacin.

Elimination: The clearance of ropinirole after oral administration to patients is 47 L/hr (cv = 45%) and its elimination half-life is approximately 6 hours. Less than 10% of the administered dose is excreted as unchanged drug in urine. N-despropyl ropinirole is the predominant metabolite found in urine (40%), followed by the carboxylic acid metabolite (10%), and the glucuronide of the hydroxy metabolite (10%).

Drug Interactions: Ciprofloxacin: Coadministration of ciprofloxacin (500 mg twice daily), an inhibitor of CYP1A2, with immediate-release ropinirole (2 mg 3 times daily) increased ropinirole AUC by 84% on average and Cmax by 60% (n = 12 patients).

Digoxin: Coadministration of immediate-release ropinirole (2 mg 3 times daily) with digoxin (0.125 to 0.25 mg once daily) did not alter the steady-state pharmacokinetics of digoxin in 10 patients.

Theophylline: Administration of theophylline (300 mg twice daily, a substrate of CYP1A2) did not alter the steady-state pharmacokinetics of immediate-release ropinirole (2 mg 3 times daily) in 12 patients with Parkinson’s disease. Immediate-release ropinirole (2 mg 3 times daily) did not alter the pharmacokinetics of theophylline (5 mg/kg IV) in 12 patients with Parkinson’s disease.

L-dopa: Coadministration of carbidopa + l-dopa (SINEMET 10/100 mg twice daily) with immediate-release ropinirole (2 mg 3 times daily) had no effect on the steady-state pharmacokinetics of ropinirole (n = 28 patients). Oral administration of immediate-release ropinirole 2 mg 3 times daily increased mean steady-state Cmax of l-dopa by 20%, but its AUC was unaffected (n = 23 patients).

Estrogens: Population pharmacokinetic analysis revealed that higher doses of estrogens (usually associated with hormone replacement therapy [HRT]) reduced the oral clearance of ropinirole by approximately 35%.

Commonly Administered Drugs: Population analysis showed that commonly administered drugs, e.g., selegiline, amantadine, tricyclic antidepressants, benzodiazepines, ibuprofen, thiazides, antihistamines, and anticholinergics, did not affect the oral clearance of ropinirole.

Population Subgroups: Because therapy with REQUIP XL is initiated at a low dose and gradually titrated upward according to clinical tolerability to obtain the optimum therapeutic effect, adjustment of the initial dose based on gender, weight, or age is not necessary.

Age: Oral clearance of ropinirole is reduced by approximately 15% in patients above 65 years of age compared with younger patients. Dosage adjustment is not necessary in the elderly (above 65 years), as the dose of ropinirole is individually titrated to clinical response.

Gender: Female and male patients showed similar oral clearance.

Race: The influence of race on the pharmacokinetics of ropinirole has not been evaluated.

Renal Impairment: Based on population pharmacokinetic analysis, no difference was observed in the pharmacokinetics of ropinirole in patients with moderate renal impairment (creatinine clearance between 30 to 50 mL/min) compared with an age-matched population with creatinine clearance above 50 mL/min. Therefore, no dosage adjustment is necessary in patients with moderate renal impairment. The use of ropinirole in patients with severe renal impairment has not been studied.

The effect of hemodialysis on ropinirole clearance is not known, but because of the relatively high apparent volume of distribution of ropinirole (7.5 L/kg), significant removal of ropinirole by hemodialysis is unlikely.

Hepatic Impairment: The pharmacokinetics of ropinirole have not been studied in patients with hepatic impairment. These patients may have higher plasma levels and lower clearance of ropinirole than patients with normal hepatic function. REQUIP XL should be titrated with caution in this population.

Other Diseases: Population pharmacokinetic analysis revealed no change in the oral clearance of ropinirole in patients with concomitant diseases such as hypertension, depression, osteoporosis/arthritis, and insomnia compared with patients who had Parkinson’s disease only.

13 NONCLINICAL TOXICOLOGY

13.1 Carcinogenesis, Mutagenesis, Impairment of Fertility

Two-year carcinogenicity studies were conducted in Charles River CD-1 mice at doses of 5, 15, and 50 mg/kg/day and in Sprague-Dawley rats at doses of 1.5, 15, and 50 mg/kg/day (top doses which, based on mg/m^2, are equivalent to 10 and 20 times, respectively, the MRHD of 24 mg/day). In the male rat, there was a significant increase in testicular Leydig cell adenomas at all doses tested, i.e., ≥1.5 mg/kg (0.6 times the MRHD on a mg/m^2 basis). This finding is of questionable significance because the endocrine mechanisms believed to be involved in the production of Leydig cell hyperplasia and adenomas in rats are not relevant to humans. In the female mouse, there was an increase in benign uterine endometrial polyps at a dose of 50 mg/kg/day (10 times the MRHD on a mg/m^2 basis).

Ropinirole was not mutagenic or clastogenic in the in vitro Ames test, the in vitro chromosome aberration test in human lymphocytes, the in vitro mouse lymphoma (L1578Y cells) assay, and the in vivo mouse micronucleus test.

When administered to female rats prior to and during mating and throughout pregnancy, ropinirole caused disruption of implantation at doses of 20 mg/kg/day (8 times the MRHD on a mg/m^2 basis) or greater. This effect is thought to be due to the prolactin-lowering effect of ropinirole. In humans, chorionic gonadotropin, not prolactin, is essential for implantation. In rat studies using low doses (5 mg/kg) during the prolactin-dependent phase of early pregnancy (gestation days 0 to 8), ropinirole did not affect female fertility at dosages up to 100 mg/kg/day (40 times the MRHD on a mg/m^2 basis). No effect on male fertility was observed in rats at dosages up to 125 mg/kg/day (50 times the MRHD on a mg/m^2 basis).

14 CLINICAL STUDIES

The effectiveness of the immediate-release formulation of ropinirole (REQUIP Tablets) in the treatment of early and advanced Parkinson’s disease was initially established in 3 randomized, double-blind, placebo-controlled trials.

The effectiveness of REQUIP XL in the treatment of Parkinson’s disease was supported by 2 randomized, double-blind, multicenter clinical trials and clinical pharmacokinetic considerations. One trial conducted in advanced Parkinson’s disease patients compared REQUIP XL with placebo as adjunctive therapy to L-dopa. A second trial compared REQUIP XL with REQUIP Tablets in early phase Parkinson’s disease patients not receiving L-dopa.

In these studies a variety of measures were used to assess the effects of treatment (e.g., patient diaries recording time “on” and “off,” tolerability of L-dopa dose reductions, and the Unified Parkinson’s Disease Rating Scale [UPDRS] scores). The UPDRS is a multi-item rating scale evaluating mentation (Part I), activities of daily living (Part II), motor performance (Part III), and complications of therapy (Part IV). Part III of the UPDRS contains 14 items designed to assess the severity of the cardinal motor findings in patients with Parkinson’s disease (e.g., tremor, rigidity, bradykinesia, postural instability, etc.) scored for different body regions and has a maximum (worst) score of 108.

14.1 Study in Patients With Advanced Parkinson’s Disease (With L-dopa)

The effectiveness of REQUIP XL as adjunctive therapy to L-dopa in patients with Parkinson’s disease was established in a randomized, double-blind, placebo-controlled, parallel group, 24-week clinical trial in 393 patients (Hoehn & Yahr criteria Stages II-IV) who were not adequately controlled by L-dopa therapy. Patients were allowed to be on concomitant selegiline, amantadine, anticholinergics, and catechol-O-methyltransferase (COMT) inhibitors provided the doses were stable for at least 4 weeks prior to screening and throughout the trial. The primary efficacy endpoint evaluated was the mean change from baseline in total awake time spent “off”.

Patients in this study had a mean disease duration of 8.6 years, a mean duration of exposure to L-dopa of 6.5 years, had experienced a minimum of 3 hours awake time “off” with a baseline average of approximately 7 hours awake time “off”, and had a mean baseline UPDRS motor score of approximately 30 points with similar mean data in each treatment group. The mean baseline dose of L-dopa in the group receiving REQUIP XL was 824 mg/day and 776 mg/day for the placebo group. Patients initiated treatment at 2 mg/day for 1 week followed by increases of 2 mg/day at weekly intervals to a minimum dose of 6 mg/day. The following week, the REQUIP XL total daily dose could be further increased (based upon therapeutic response and tolerability) to 8 mg/day. Once a daily dose of 8 mg/day was reached, the background L-dopa dosage was reduced. Thereafter, the daily dose could be increased by up to 4 mg/day approximately every 2 weeks until an optimal dose was achieved (based upon therapeutic response and tolerability). The mean dose of REQUIP XL at the end of Week 24 was 18.8 mg/day. Dose titrations were based upon the degree of symptom control, planned L-dopa dosage reduction, and/or tolerability. The maximal allowed daily dosage for REQUIP XL was 24 mg/day.

The primary efficacy endpoint was mean change from baseline in total awake time spent “off” at Week 24. At baseline the mean total awake time spent “off” was approximately 7 hours in each treatment group. At Week 24, the total awake time spent “off”, on average, had decreased by approximately 2 hours in the group receiving REQUIP XL and by approximately half an hour in the placebo group. The adjusted mean difference in total awake time spent “off” between REQUIP XL and placebo was -1.7 hours, which was statistically significant (ANCOVA, p< 0.0001). Results for this endpoint showing the statistical superiority of REQUIP XL over Placebo are presented in Table 3.

Table 3. Change from Baseline in Total Awake Time Spent “Off” at Week 24
 | REQUIP XL (n = 201) | Placebo (n = 190)
Mean “Off” time at Baseline (hours) | 7.0 | 7.0
Mean Change from Baseline in “Off” time (hours) | -2.1 | -0.4

The difference between groups in favor of REQUIP XL, with regard to a decrease in total “off” hours, was primarily related to an increase in total “on” hours without troublesome dyskinesia. Patients treated with REQUIP XL had a mean reduction in L-dopa dose of 278 mg/day (34%) while patients treated with placebo had a mean reduction of 164 mg/day (21%). In patients who reduced their L-dopa dose, reduction was sustained in 93% of patients treated with REQUIP XL and in 72% of patients treated with placebo (p<0.001).

14.2 Study in Patients With Early Parkinson’s Disease (Without L-dopa)

A 36-week multicenter, double-blind, titration/3-period maintenance, cross-over study compared the efficacy of REQUIP XL with the immediate-release formulation of REQUIP (IR) in 161 patients with early phase Parkinson’s disease (Hoehn & Yahr Stages I-III) with limited prior exposure to L-dopa or dopamine agonists. Eligible subjects were randomized (1:1:1:1) to 4 treatment sequences (2 were titrated on REQUIP IR and 2 on REQUIP XL). The REQUIP IR titration was slower in rate than that of the REQUIP XL. Patients were titrated, during the 12-week titration period, to their optimal dosage, based upon tolerance and therapeutic response. This was followed by 3 consecutive 8-week maintenance periods, during which patients were either maintained on the prior formulation or switched to the alternative formulation. All switches were performed overnight by using the approximately equivalent doses of ropinirole. The primary efficacy endpoint was the change of UPDRS motor score within each maintenance period.

Patients in all 4 groups started out with similar UPDRS motor scores (about 21) at baseline. All 4 groups exhibited similar improvement in UPDRS total motor scores from baseline until the completion of the titration phase, with a change in score of about -9 observed for the groups started on REQUIP IR and of about -10 for the groups started on REQUIP XL. No difference was observed between groups when switches were made between identical formulations or between different formulations. This suggests therapeutic dosage equivalence between REQUIP IR and REQUIP XL formulations.

The optimal daily dose at the end of the titration period for patients on REQUIP IR was substantially lower (mean 7 mg) compared to the dose at the end of the titration period for patients on REQUIP XL (mean 18 mg). In this study, the marked difference in the final optimal dosages suggests that the higher doses afforded no additional benefit when compared to the lower doses [see Dosage and Administration (2)].

16 HOW SUPPLIED/STORAGE AND HANDLING

Each biconvex, capsule-shaped, film-coated tablet contains ropinirole hydrochloride equivalent to the labeled amount of ropinirole as follows:

- 2 mg: pink tablets debossed with “GS” and “3V2”, in bottles of 30 (NDC 54868-6093-0).

Storage: Store at 25°C (77°F); excursions permitted to 15-30°C (59-86°F) [see USP Controlled Room Temperature].

Dispense in a tight, light-resistant container as defined in the USP.

17 PATIENT COUNSELING INFORMATION

See FDA-Approved Patient Labeling (17.9)

Physicians should instruct their patients to read the Patient Information leaflet before starting therapy with REQUIP XL and to reread it upon prescription renewal for new information regarding the use of REQUIP XL.

17.1 Dosing Instructions

- Patients should be instructed to take REQUIP XL only as prescribed. If a dose is missed, patients should be advised not to double their next dose.
- REQUIP XL can be taken with or without food. Taking REQUIP XL with food may reduce the occurrence of nausea [see Dosage and Administration (2.1)].
- REQUIP XL Tablets should be swallowed whole. They should not be chewed, crushed, or divided [see Dosage and Administration (2.1)].
- Ropinirole is the active ingredient that is in both REQUIP XL and REQUIP Tablets (the immediate-release formulation). Ask your patient if they are taking another medication containing ropinirole.

17.2 Postural (Orthostatic) Hypotension

Patients should be advised that they may develop postural (orthostatic) hypotension with or without symptoms such as dizziness, nausea, syncope, and sometimes sweating. Hypotension and/or orthostatic symptoms may occur more frequently during initial therapy or with an increase in dose at any time (cases have been seen after weeks of treatment). Accordingly, patients should be cautioned against standing up rapidly after sitting or lying down, especially if they have been doing so for prolonged periods, and especially at the initiation of treatment with REQUIP XL [see Warnings and Precautions (5.2, 5.3)].

17.3 Elevation of Blood Pressure and Changes in Heart Rate

Patients should be alerted to the possibility of increases in blood pressure during treatment with REQUIP XL. Exacerbation of hypertension may occur. Medication dose adjustment may be necessary if elevation of blood pressure is sustained over multiple evaluations. Patients with cardiovascular disease, who may not tolerate marked changes in heart rate, should also be alerted to the possibility that they may experience significant increases or decreases in heart rate during treatment with REQUIP XL [see Warnings and Precautions (5.4)].

17.4 Sedating Effects

Patients should be alerted to the potential sedating effects caused by REQUIP XL, including somnolence and the possibility of falling asleep while engaged in activities of daily living. Since somnolence is a frequent adverse reaction with potentially serious consequences, patients should neither drive a car nor engage in other potentially dangerous activities until they have gained sufficient experience with REQUIP XL to gauge whether or not it affects their mental and/or motor performance adversely. Patients should be advised that if increased somnolence or episodes of falling asleep during activities of daily living (e.g., conversations, eating, driving a motor vehicle, etc.) are experienced at any time during treatment, they should not drive or participate in potentially dangerous activities until they have contacted their physician.

Because of possible additive effects, caution should be advised when patients are taking other sedating medications, alcohol, or other CNS depressants (e.g., benzodiazepines, antipsychotics, antidepressants, etc.) in combination with REQUIP XL or when taking concomitant medications that increase plasma levels of ropinirole (e.g., ciprofloxacin) [see Warnings and Precautions (5.1)].

17.5 Hallucinations

Patients should be informed they may experience hallucinations (unreal visions, sounds, or sensations) while taking ropinirole. The elderly are at greater risk than younger patients with Parkinson's disease; and the risk is greater in patients who are taking ropinirole with L-dopa or taking higher doses of ropinirole, and may also be further increased in patients taking any other drugs that increase dopaminergic tone [see Warnings and Precautions (5.5)].

17.6 Impulse Control Symptoms Including Compulsive Behaviors

There have been reports of patients experiencing intense urges to gamble, increased sexual urges, and other intense urges and the inability to control these urges while taking one or more of the medications that increase central dopaminergic tone, that are generally used for the treatment of Parkinson’s disease or Restless Legs Syndrome, including ropinirole. In the clinical development program (N = 613), 6 patients treated with REQUIP XL exhibited compulsive behaviors consisting of pathological gambling and/or hypersexuality. Although it is not proven that the medications caused these events, these urges were reported to have stopped in some cases when the dose was reduced or the medication was stopped. Prescribers should ask patients about the development of new or increased gambling urges, sexual urges or other urges while being treated with REQUIP XL. Patients should inform their physician if they experience new or increased gambling urges, increased sexual urges or other intense urges while taking REQUIP XL. Physicians should consider dose reduction or stopping the medication if a patient develops such urges while taking REQUIP XL.

17.7 Nursing Mothers

Because of the possibility that ropinirole may be excreted in breast milk, a decision should be made whether to discontinue nursing or to discontinue the drug, taking into account the importance of the drug to the mother [see Use in Specific Populations (8.3)].

Patients should be advised that ropinirole could inhibit lactation, as ropinirole inhibits prolactin secretion.

17.8 Pregnancy

Because ropinirole has been shown to have adverse effects on embryo-fetal development, including teratogenic effects, in animals, and because experience in humans is limited, patients should be advised to notify their physician if they become pregnant or intend to become pregnant during therapy [see Use in Specific Populations (8.1)].

17.9 FDA-Approved Patient Labeling

Patient labeling is provided as a tear-off leaflet at the end of this full prescribing information.

Physicians should instruct their patients to read the Patient Information leaflet before starting therapy with REQUIP XL and to reread it upon prescription renewal for new information regarding the use of REQUIP XL.

REQUIP XL is a trademark of GlaxoSmithKline.

*SINEMET is a registered trademark of Merck & Co., Inc.

GlaxoSmithKline

Research Triangle Park, NC 27709

©2009, GlaxoSmithKline. All rights reserved.

Additional barcode label applied by:

Physicians Total Care, Inc.

Tulsa, Oklahoma 74146

PHARMACIST--DETACH HERE AND GIVE INSTRUCTIONS TO PATIENT

_ _ _ _ _ _ _ _ _ _ _ _ _ _ _ _ _ _ _ _ _ _ _ _ _ _ _ _ _ _ _ _ _ _ _ _ _ _ _ _ _ _ _ _ _ _ _

PATIENT INFORMATION

REQUIP® (RE-qwip) (ropinirole) Tablets

REQUIP® XL™ (RE-qwip)

(ropinirole extended-release tablets)

IF YOU HAVE PARKINSON’S DISEASE, READ THIS SIDE

IF YOU HAVE RESTLESS LEGS SYNDROME, READ THE OTHER SIDE

IMPORTANT NOTE: REQUIP XL has not been studied in Restless Legs Syndrome (RLS) and is not approved for the treatment of RLS. However, an immediate-release form of ropinirole (REQUIP) is approved for the treatment of RLS (see other side of this leaflet).

Read this information completely before you start taking REQUIP or REQUIP XL. Read the information each time you get more medicine. There may be new information. This leaflet provides a summary about REQUIP and REQUIP XL. It does not include everything there is to know about your medicine. This information should not take the place of discussions with your healthcare provider about your medical condition or treatment with REQUIP or REQUIP XL.

What are REQUIP and REQUIP XL?

REQUIP is a short-acting prescription medicine containing ropinirole (usually taken 3 times a day) used to treat Parkinson's disease. It is also used to treat a condition called Restless Legs Syndrome.

REQUIP XL is a long-acting prescription medicine containing ropinirole (taken once a day) used to treat Parkinson’s disease.

You should not be taking more than one medicine containing ropinirole. Inform your physician if you are taking any other medicine containing ropinirole.

REQUIP and REQUIP XL have not been studied in children.

What is the most important information I should know about REQUIP and REQUIP XL?

REQUIP and REQUIP XL can cause serious side effects including:

- Falling asleep during normal activities. You may fall asleep while doing normal activities such as driving a car, doing physical tasks, or using hazardous machinery while taking REQUIP or REQUIP XL. You may suddenly fall asleep without being drowsy or without warning. This may result in having accidents. Your chances of falling asleep while doing normal activities while taking REQUIP or REQUIP XL are greater if you take other medicines that cause drowsiness. Tell your healthcare provider right away if this happens. Before starting REQUIP or REQUIP XL, be sure to tell your healthcare provider if you take any medicines that make you drowsy.
- Changes in blood pressure. REQUIP and REQUIP XL can decrease or increase your blood pressure. Lowering of your blood pressure is of special concern. If you faint, feel dizzy, nauseated, or sweaty when you stand up from sitting or lying down, this may mean that your blood pressure is decreased. If you notice this, you should contact your healthcare provider. Also, when changing position from lying down or sitting to standing up, you should do it carefully and slowly. Lowering of your blood pressure can happen especially when you start taking REQUIP or REQUIP XL or when your dose is increased.
- Fainting. Fainting can occur, and sometimes your heart rate may be decreased. This can happen especially when you start taking REQUIP or REQUIP XL or your dose is increased. Tell your healthcare provider if you faint or feel dizzy.
- Hallucinations (unreal visions, sounds, or sensations) can occur in patients taking REQUIP or REQUIP XL. The chances of having hallucinations are higher in patients with Parkinson's disease who are elderly, taking REQUIP or REQUIP XL with other Parkinson’s disease drugs, or taking higher doses of REQUIP or REQUIP XL. If you have hallucinations, talk with your healthcare provider.
- Uncontrolled sudden movements. REQUIP or REQUIP XL may cause uncontrolled sudden movements or make such movements you already have worse or more frequent. Tell your healthcare provider if this happens. The doses of your anti-Parkinson’s medicines may need to be changed.

Unusual urges. Some patients taking REQUIP or REQUIP XL get urges to behave in a way unusual for them. Examples of this are an unusual urge to gamble or increased sexual urges and behaviors. If you notice or your family notices that you are developing any unusual behaviors, talk to your healthcare provider.

See “What are the possible side effects of REQUIP and REQUIP XL?”

What should I tell my healthcare provider before taking REQUIP or REQUIP XL?

Be sure to tell your healthcare provider if you:

- have daytime sleepiness from a sleep disorder or have unexpected or unpredictable sleepiness or periods of sleep.
- are taking any other prescription or over-the-counter medicines. Some of these medicines may increase your chances of getting side effects while taking REQUIP or REQUIP XL.
- start or stop taking other medicines while you are taking REQUIP or REQUIP XL. This may increase your chances of getting side effects.
- start or stop smoking while you are taking REQUIP or REQUIP XL. Smoking may decrease the treatment effect of REQUIP or REQUIP XL.
- feel dizzy, nauseated, sweaty, or faint when you first stand up from sitting or lying down.
- drink alcoholic beverages. This may increase your chances of becoming drowsy or sleepy while taking REQUIP or REQUIP XL.
- have high or low blood pressure.
- are pregnant or plan to become pregnant. REQUIP and REQUIP XL should only be used during pregnancy if needed.
- are breastfeeding. It is not known if REQUIP or REQUIP XL passes into your breast milk. Talk to your healthcare provider to decide whether you will breastfeed or take REQUIP or REQUIP XL.
- are allergic to any of the ingredients in REQUIP or REQUIP XL. See the end of this Patient Information leaflet for a complete list of the ingredients in REQUIP and REQUIP XL.

How should I take REQUIP or REQUIP XL for Parkinson's disease?

- Take REQUIP or REQUIP XL exactly as directed by your healthcare provider.
- Do not suddenly stop taking REQUIP or REQUIP XL without talking to your healthcare provider. If you stop this medicine suddenly, you may develop fever, confusion, or severe muscle stiffness.
- Before starting REQUIP or REQUIP XL, you should talk to your healthcare provider about what to do if you miss a dose. If you have missed the previous dose and it is time for your next dose, do not double the dose.
- Your healthcare provider will start you on a low dose of REQUIP or REQUIP XL. Your healthcare provider will change the dose until you are taking the right amount of medicine to control your symptoms. It may take several weeks before you reach a dose that controls your symptoms.

If you are taking REQUIP:

- REQUIP Tablets are usually taken 3 times each day for Parkinson's disease.

If you are taking REQUIP XL:

- Take REQUIP XL Tablets 1 time each day for Parkinson’s disease, preferably at or around the same time of day.
- Swallow REQUIP XL Tablets whole. Do not chew, crush, or split REQUIP XL Tablets.

If you are taking either REQUIP or REQUIP XL:

- Contact your healthcare provider if you stop taking REQUIP or REQUIP XL for any reason. Do not restart without talking with your healthcare provider.
- Your healthcare provider may prescribe REQUIP or REQUIP XL alone, or add REQUIP or REQUIP XL to medicine that you are already taking for Parkinson's disease.
- You should not substitute REQUIP for REQUIP XL or REQUIP XL for REQUIP without talking with your healthcare provider.
- You can take REQUIP or REQUIP XL with or without food. If you experience nausea you may try taking REQUIP or REQUIP XL with food.

What are the possible side effects of REQUIP and REQUIP XL?

Serious side effects in people taking REQUIP and REQUIP XL are described in the section “REQUIP and REQUIP XL can cause serious side effects including” and include:

- Falling asleep during normal activities
- Changes in blood pressure
- Fainting
- Hallucinations
- Uncontrolled sudden movements

Some patients taking REQUIP or REQUIP XL get urges to behave in a way unusual for them. Examples of this are an unusual urge to gamble or increased sexual urges and behaviors. If you notice or your family notices that you are developing any unusual behaviors, talk to your healthcare provider.

You should be careful until you know if REQUIP or REQUIP XL affects your ability to remain alert while doing normal daily activities, driving a car, operating machinery, or working at heights. You should also watch for the development of significant daytime sleepiness or episodes of falling asleep.

Common side effects in people taking REQUIP and REQUIP XL include:

- Fainting
- Sleepiness
- Hallucinations
- Dizziness
- Nausea or vomiting
- Uncontrolled sudden movements
- Leg swelling
- Fatigue
- Headache
- Upset stomach
- Increased sweating

This is not a complete list of side effects and should not take the place of discussions with your healthcare providers. Your healthcare provider or pharmacist can give you a more complete list of possible side effects.

Call your healthcare provider for medical advice about side effects. You may report side effects to FDA at 1-800-FDA-1088.

How should I store REQUIP and REQUIP XL?

- Store REQUIP Tablets between 68°-77°F (20°-25°C).
- Store REQUIP XL Tablets between 59°-86°F (15°-30°C).
- Store REQUIP or REQUIP XL at room temperature out of direct sunlight.
- Keep REQUIP or REQUIP XL in a tightly closed container.
- Keep REQUIP or REQUIP XL out of the reach of children.

Other Information about REQUIP and REQUIP XL:

- Do not share REQUIP or REQUIP XL with other people, even if they have the same symptoms you have.
- Studies of people with Parkinson’s disease show that they may be at an increased risk of developing melanoma, a form of skin cancer, when compared to people without Parkinson’s disease. It is not known if this problem is associated with Parkinson’s disease or the medicines used to treat Parkinson’s disease. REQUIP and REQUIP XL are two of the medicines used to treat Parkinson’s disease, therefore, patients being treated with REQUIP or REQUIP XL should have periodic skin examinations.

This patient information leaflet summarizes the most important information about REQUIP and REQUIP XL for Parkinson’s disease. Medicines are sometimes prescribed for purposes other than those listed in this leaflet. Do not take REQUIP or REQUIP XL for a condition for which it was not prescribed. For more information, talk with your healthcare provider or pharmacist. They can give you information about REQUIP and REQUIP XL that is written for healthcare professionals. For more information call 1-888-825-5249 (toll-free) or visit www.requipxl.com.

What are the ingredients in REQUIP and REQUIP XL?

The following ingredients are in REQUIP:

Active ingredient: ropinirole (as ropinirole hydrochloride)

Inactive ingredients: croscarmellose sodium, hydrous lactose, magnesium stearate, microcrystalline cellulose, and one or more of the following: carmine, FD&C Blue No. 2 aluminum lake, FD&C Yellow No. 6 aluminum lake, hypromellose, iron oxides, polyethylene glycol, polysorbate 80, titanium dioxide.

The following ingredients are in REQUIP XL:

Active ingredient: ropinirole (as ropinirole hydrochloride)

Inactive ingredients: carboxymethylcellulose sodium, colloidal silicon dioxide, glycerol behenate, hydrogenated castor oil, hypromellose, lactose monohydrate, magnesium stearate, maltodextrin, mannitol, povidone, and one or more of the following: FD&C Yellow No. 6 aluminum lake, FD&C Blue No. 2 aluminum lake, ferric oxides (black, red, yellow), polyethylene glycol 400, titanium dioxide.

PATIENT INFORMATION

REQUIP® (RE-qwip) (ropinirole) Tablets

IF YOU HAVE RESTLESS LEGS SYNDROME (RLS), READ THIS SIDE

IF YOU HAVE PARKINSON’S DISEASE, READ THE OTHER SIDE

Read this information completely before you start taking REQUIP. Read the information each time you get more medicine. There may be new information. This leaflet provides a summary about REQUIP. It does not include everything there is to know about your medicine. This information should not take the place of discussions with your healthcare provider about your medical condition or treatment with REQUIP.

Patients with RLS should take REQUIP differently than patients with Parkinson’s disease (see How should I take REQUIP for RLS? for the recommended dosing for RLS). A lower dose of REQUIP is generally needed for patients with RLS, and is taken once daily before bedtime.

What is the most important information I should know about REQUIP?

REQUIP can cause serious side effects including:

- Falling asleep during normal activities. You may fall asleep while doing normal activities such as driving a car, doing physical tasks, or using hazardous machinery while taking REQUIP. You may suddenly fall asleep without being drowsy or without warning. This may result in having accidents. Your chances of falling asleep while doing normal activities while taking REQUIP are greater if you take other medicines that cause drowsiness. Tell your healthcare provider right away if this happens. Before starting REQUIP, be sure to tell your healthcare provider if you take any medicines that make you drowsy.
- Decrease in blood pressure. REQUIP can decrease your blood pressure. Lowering of your blood pressure is of special concern. If you faint, feel dizzy, nauseated, or sweaty when you stand up from sitting or lying down, this may mean that your blood pressure is decreased. If you notice this, you should contact your healthcare provider. Also, when changing position from lying down or sitting to standing up, you should do it carefully and slowly. Lowering of your blood pressure can happen especially when you start taking REQUIP or when your dose is increased.
- Fainting. Fainting can occur, and sometimes your heart rate may be decreased. This can happen especially when you start taking REQUIP or your dose is increased. Tell your healthcare provider if you faint or feel dizzy.
- Hallucinations (unreal visions, sounds, or sensations) can occur in patients taking REQUIP. If you have hallucinations, talk with your healthcare provider.

Unusual urges. Some patients taking REQUIP get urges to behave in a way unusual for them. Examples of this are an unusual urge to gamble or increased sexual urges and behaviors. If you notice or your family notices that you are developing any unusual behaviors, talk to your healthcare provider.

See “What are the possible side effects of REQUIP?”

What is REQUIP?

REQUIP is a prescription medicine containing ropinirole used to treat moderate-to-severe primary Restless Legs Syndrome. It is also used to treat Parkinson's disease. Having one of these conditions does not mean you have or will develop the other.

REQUIP has not been studied in children.

What should I tell my healthcare provider before taking REQUIP?

Be sure to tell your healthcare provider if you:

- have daytime sleepiness from a sleep disorder or have unexpected or unpredictable sleepiness or periods of sleep.
- are taking any other prescription or over-the-counter medicines. Some of these medicines may increase your chances of getting side effects while taking REQUIP.
- start or stop taking other medicines while you are taking REQUIP. This may increase your chances of getting side effects.
- start or stop smoking while you are taking REQUIP. Smoking may decrease the treatment effect of REQUIP.
- feel dizzy, nauseated, sweaty, or faint when you first stand up from sitting or lying down.
- drink alcoholic beverages. This may increase your chances of becoming drowsy or sleepy while taking REQUIP.
- have high or low blood pressure.
- are pregnant or plan to become pregnant. REQUIP should only be used during pregnancy if needed.
- are breastfeeding. It is not known if REQUIP passes into your breast milk. Talk to your healthcare provider to decide whether you will breastfeed or take REQUIP.
- are allergic to any of the ingredients in REQUIP. See the end of this Patient Information leaflet for a complete list of the ingredients in REQUIP.

How should I take REQUIP for RLS?

- Take REQUIP exactly as directed by your healthcare provider.
- The usual way to take REQUIP is once in the evening, 1 to 3 hours before bedtime.
- Your healthcare provider will start you on a low dose of REQUIP. Your healthcare provider may change the dose until you are taking the right amount of medicine to control your symptoms.
- If you miss your dose, do not double your next dose. Take only your usual dose 1 to 3 hours before your next bedtime.
- Contact your healthcare provider if you stop taking REQUIP for any reason. Do not restart without consulting your healthcare provider.
- You can take REQUIP with or without food. Taking REQUIP with food may decrease the chances of feeling nauseated.

What are the possible side effects of REQUIP?

Serious side effects in people taking REQUIP are described in the section “REQUIP can cause serious side effects including” and include:

- Falling asleep during normal activities
- Decrease in blood pressure
- Fainting
- Hallucinations

Some patients taking REQUIP get urges to behave in a way unusual for them. Examples of this are an unusual urge to gamble or increased sexual urges and behaviors. If you notice or your family notices that you are developing any unusual behaviors, talk to your healthcare provider.

You should be careful until you know if REQUIP affects your ability to remain alert while doing normal daily activities, driving a car, operating machinery, or working at heights. You should also watch for the development of significant daytime sleepiness or episodes of falling asleep.

Common side effects in people taking REQUIP include:

- Nausea or vomiting
- Sleepiness or drowsiness
- Dizziness
- Fatigue

This is not a complete list of side effects and should not take the place of discussions with your healthcare providers. Your healthcare provider or pharmacist can give you a more complete list of possible side effects.

Call your healthcare provider for medical advice about side effects. You may report side effects to FDA at 1-800-FDA-1088.

How should I store REQUIP?

- Store REQUIP Tablets between 68°-77°F (20°-25°C).
- Store REQUIP at room temperature out of direct sunlight.
- Keep REQUIP in a tightly closed container.
- Keep REQUIP out of the reach of children.

Other Information about REQUIP

- Do not share REQUIP with other people, even if they have the same symptoms you have.
- Studies of people with Parkinson’s disease show that they may be at an increased risk of developing melanoma, a form of skin cancer, when compared to people without Parkinson’s disease. It is not known if this problem is associated with Parkinson’s disease or the medicines used to treat Parkinson’s disease. REQUIP is one of the medicines used to treat Parkinson’s disease, therefore, patients being treated with REQUIP should have periodic skin examinations.

This patient information leaflet summarizes important information about REQUIP for Restless Legs Syndrome. Medicines are sometimes prescribed for purposes other than those listed in this leaflet. Do not take REQUIP for a condition for which it was not prescribed. For more information, talk with your healthcare provider or pharmacist. They can give you information about REQUIP that is written for healthcare professionals. For more information call 1-888-825-5249 (toll-free) or visit www.requip.com.

What are the ingredients in REQUIP?

The following ingredients are in REQUIP:

Active ingredient: ropinirole (as ropinirole hydrochloride)

Inactive ingredients: croscarmellose sodium, hydrous lactose, magnesium stearate, microcrystalline cellulose, and one or more of the following: carmine, FD&C Blue No. 2 aluminum lake, FD&C Yellow No. 6 aluminum lake, hypromellose, iron oxides, polyethylene glycol, polysorbate 80, titanium dioxide.

GlaxoSmithKline

Research Triangle Park, NC 27709

©2008, GlaxoSmithKline. All rights reserved.

RXL:2PIL

July 2008

PACKAGE LABEL

Principal Display Panel

REQUIP® XLTM

(ropinirole extended-release tablets)

2 mg

Rx only

30 Tablets

Each tablet contains 2.28 mg ropinirole HCl equivalent to 2 mg ropinirole.

Dosage: See Prescribing Information for complete dosing instructions.

Do not use if safety seal under cap is broken or missing.

Store at 25oC (77oF); excursions permitted to 15-30oC (59-86oF) [see USP Controlled Room Temperature].